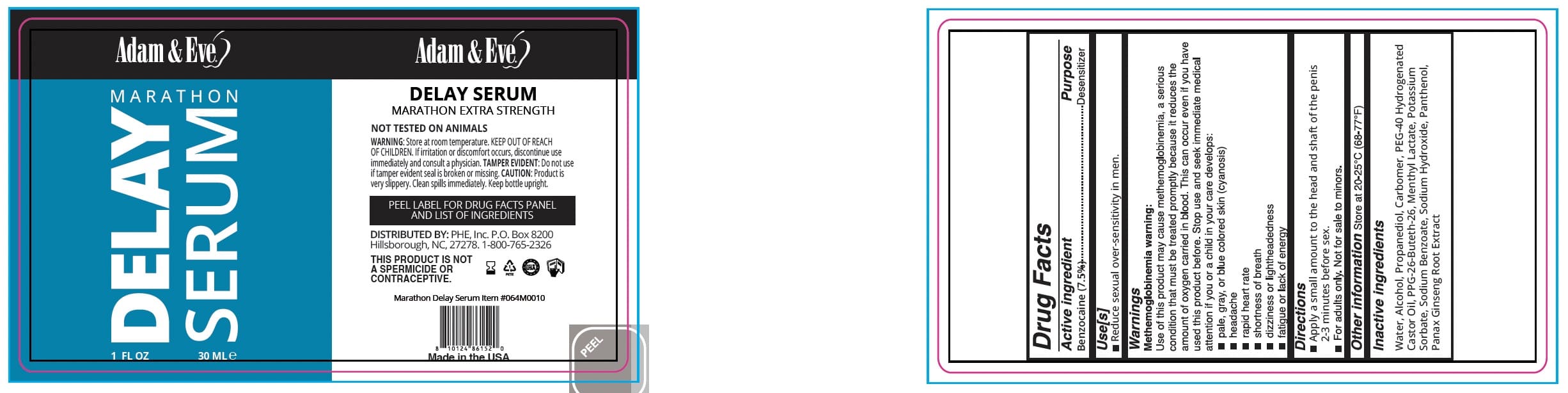 DRUG LABEL: A and E Marathon Delay Serum
NDC: 87068-181 | Form: CREAM
Manufacturer: Phe Inc
Category: otc | Type: HUMAN OTC DRUG LABEL
Date: 20251111

ACTIVE INGREDIENTS: BENZOCAINE 7.5 mg/100 mL
INACTIVE INGREDIENTS: PANTHENOL; POTASSIUM SORBATE; WATER; CARBOMER HOMOPOLYMER, UNSPECIFIED TYPE; POLYOXYL 40 HYDROGENATED CASTOR OIL; MENTHYL LACTATE, (-)-; PROPANEDIOL; PPG-26-BUTETH-26; SODIUM BENZOATE; ALCOHOL; ASIAN GINSENG; SODIUM HYDROXIDE

PHE-PLP A&E Marathon Delay Serum

Active Ingredient(s)

Benzocaine (7.5%)

Purpose

Desensitizer

Use

Reduce sexual over-sensitivity in men.

Warnings

Methemoglobinemia warning: Use of this product may cause methemoglobinemia, a serious condition that must be treated promptly because it reduces the amount of oxygen carried in blood. This can occur even if you have used this product before. Stop use and seek immediate medical attention if you or a child in your care develops: ■ pale, gray, or blue colored skin (cyanosis) ■ headache ■ rapid heart rate ■ shortness of breath ■ dizziness or lightheadedness ■ fatigue or lack of energy

KEEP OUT OF REACH OF CHILDREN

Keep out of reach of childeren. Contact a Poison Control Center: This is the emergency contact for accidental overdose or ingestion

Directions

■ Apply a small amount to the head and shaft of the penis ■ 2-3 minutes before sex. ■ For adults only. Not for sale to minors.

Other information

Store at 20-25°C (68-77°F)

Inactive ingredients

Water, Alcohol, Propanediol, Carbomer, PEG-40 Hydrogenated Castor Oil, PPG-26-Buteth-26, Menthyl Lactate, Potassium Sorbate, Sodium Benzoate, Sodium Hydroxide, Panthenol, Panax Ginseng Root Extract